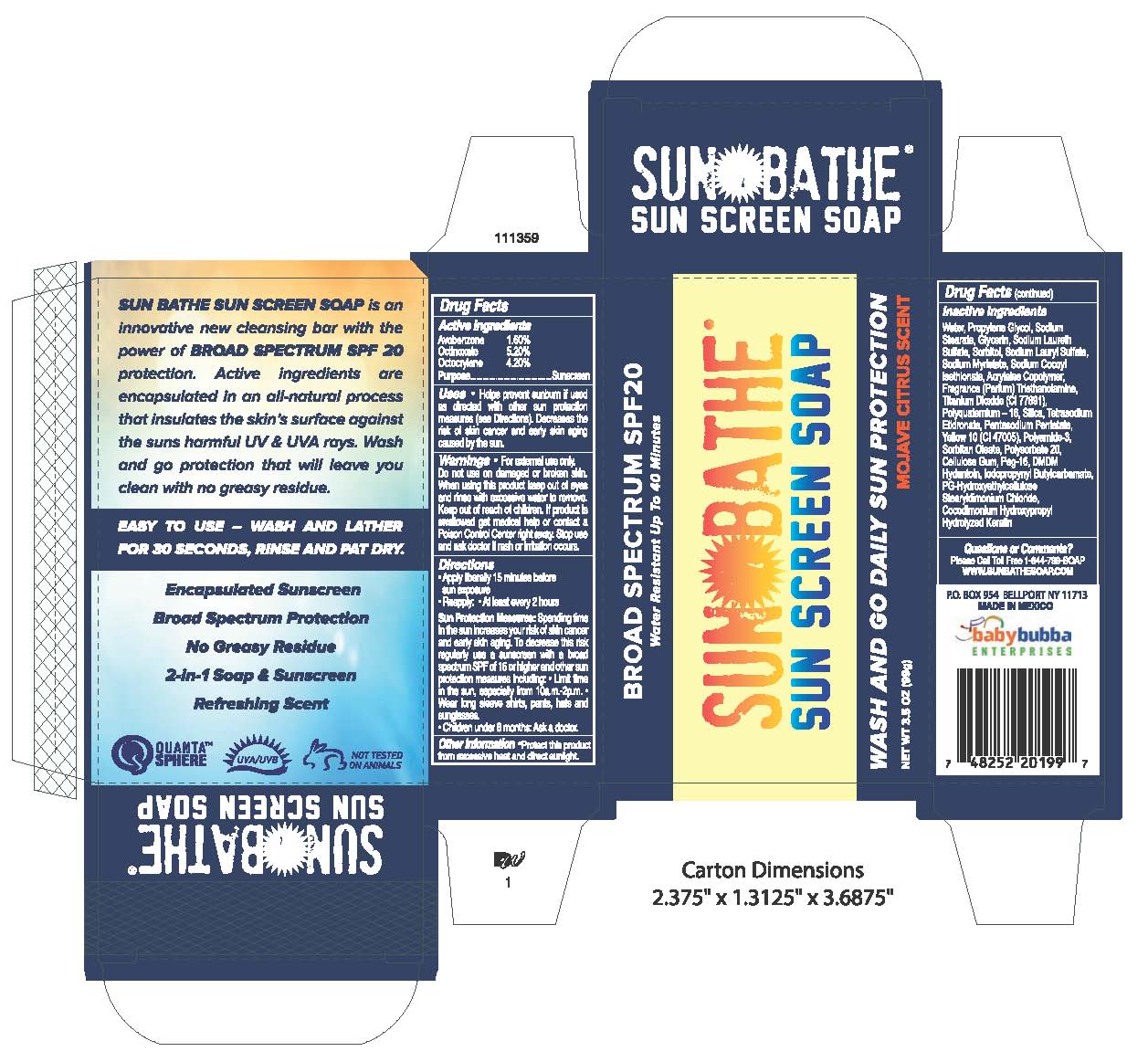 DRUG LABEL: SUN BATHE SUNSCREEN
NDC: 70342-102 | Form: SOAP
Manufacturer: BABY BUBBA ENTERPRISES INC
Category: otc | Type: HUMAN OTC DRUG LABEL
Date: 20170619

ACTIVE INGREDIENTS: AVOBENZONE 1.6 g/100 g; OCTINOXATE 5.2 g/100 g; OCTOCRYLENE 4.2 g/100 g
INACTIVE INGREDIENTS: WATER; PROPYLENE GLYCOL; SODIUM STEARATE; GLYCERIN; SODIUM LAURETH SULFATE; SORBITOL; SODIUM LAURYL SULFATE; SODIUM MYRISTATE; SODIUM COCOYL ISETHIONATE; CARBOMER COPOLYMER TYPE A; TROLAMINE; TITANIUM DIOXIDE; POLYQUATERNIUM-16 (N-VINYLPYRROLIDINONE:3-METHYL-1-VINYLIMIDAZOLIUM CHLORIDE (5:5)); SILICON DIOXIDE; EDETATE SODIUM; PENTASODIUM PENTETATE; D&C YELLOW NO. 10; POLYAMIDE-3 (30000 MW); SORBITAN MONOOLEATE; POLYSORBATE 20; CARBOXYMETHYLCELLULOSE SODIUM, UNSPECIFIED FORM; POLYETHYLENE GLYCOL 800; DMDM HYDANTOIN; IODOPROPYNYL BUTYLCARBAMATE; PROPYLENE GLYCOL-HYDROXYETHYLCELLULOSE STEARYLDIMONIUM CHLORIDE

ACTIVE INGREDIENTS

AVOBENZONE 1.6%

OCTINOXATE 5.2%

OCTOCRYLENE 4.2%

PURPOSE

SUNSCREEN

USES

- HELPS PREVENT SUNBURN
- IF USED AS DIRECTED WITH OTHER SUN PROTECTION MEASURES (SEE DIRECTIONS). DECREASES THE RISK OF SKIN CANCER AND EARLY SKIN AGING CAUSED BY THE SUN.

WARNINGS

- FOR EXTERNAL USE ONLY
- DO NOT USE ON DAMAGED OR BROKEN SKIN. WHEN USING THIS PRODUCT KEEP OUT OF EYES AND RINSE WITH EXCESSIVE WATER TO REMOVE.

KEEP OUT OF REACH OF CHILDREN. IF PRODUCT IS SWALLOWED GET MEDICAL HELP OR CONTACT A POISON CONTROL CENTER RIGHT AWAY.

STOP USE AND ASK A DOCTOR IF RASH OR IRRITATION OCCURS.

DIRECTIONS

- APPLY LIBERALLY 15 MINUTES BEFORE SUN EXPOSURE
- REAPPLY:
- AT LEAST EVERY 2 HOURS

SUN PROTECTION MEASURES: SPENDING TIME IN THE SUN INCREASES YOUR RISK OF SKIN CANCER AND EARLY SKIN AGING. TO DECREASE THIS RISK REGULARLY USE A SUNSCREEN WITH A BROAD SPECTRUM SPF OR HIGHER AND OTHER SUN PROTECTION MEASURES INCLUDING:

- LIMIT TIME IN THE SUN, ESPECIALLY FROM 10 A.M. - 2 P.M.
- WEAR LONG SLEEVE SHIRTS, PANTS, HATS AND SUNGLASSES.

- CHILDREN UNDER 6 MONTHS: ASK A DOCTOR.

OTHER INFORMATION

- PROTECT THIS PRODUCT FROM EXCESSIVE HEAT AND DIRECT SUNLIGHT.

INACTIVE INGREDIENTS

WATER, PROPYLENE GLYCOL, SODIUM STEARATE, GLYCERIN, SODIUM LAURETH SULFATE, SORBITOL, SODIUM LAURYL SULFATE, SODIUM MYRISTATE, SODIUM COCOYL ISETHIONATE, ACRYLATES COPOLYMER, FRAGRANCE (PARFUM), TRIETHANOLAMINE, TITANIUM DIOXIDE (CI 77891), POLYQUATERNIUM-16, SILICA, TETRASODIUM ETIDRONATE, PENTASODIUM PENTETATE, YELLOW 10 (CI 47005), POLYAMIDE-3, SORBITAN OLEATE, POLYSORBATE 20, CELLULOSE GUM, PEG-16, DMDM HYDANTOIN, IODOPROPYNYL BUTYLCARBAMATE, PG-HYDROXYETHYLCELLULOSE STEARYLDIMONIUM CHLORIDE, COCODIMONIUM HYDROXYPROPYL HYDROLYZED KERATIN.

QUESTIONS OR COMMENTS?

PLEASE CALL TOLL FREE 1-844-799-SOAP

WWW.SUNBATHESOAP.COM